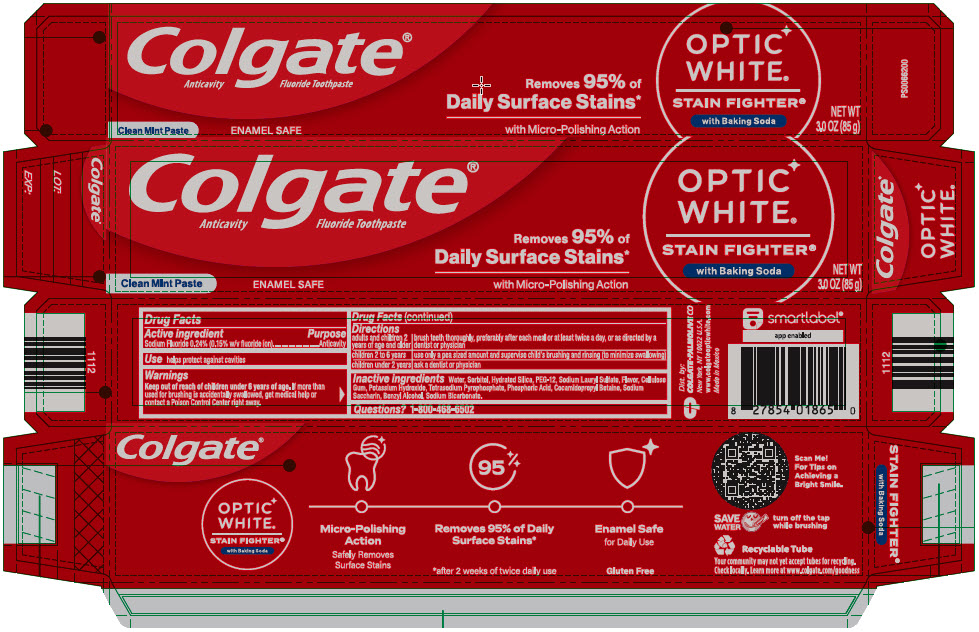 DRUG LABEL: Colgate Optic White Stain Fighter
NDC: 35000-809 | Form: PASTE, DENTIFRICE
Manufacturer: Colgate-Palmolive Company
Category: otc | Type: HUMAN OTC DRUG LABEL
Date: 20240531

ACTIVE INGREDIENTS: SODIUM FLUORIDE 1.1 mg/1 g
INACTIVE INGREDIENTS: WATER; HYDRATED SILICA; SORBITOL; GLYCERIN; POLYETHYLENE GLYCOL 600; SODIUM TRIPOLYPHOSPHATE ANHYDROUS; POTASSIUM PYROPHOSPHATE; SODIUM LAURYL SULFATE; COCAMIDOPROPYL BETAINE; SACCHARIN SODIUM; XANTHAN GUM; SODIUM HYDROXIDE; SODIUM BICARBONATE

Colgate®
Optic White® Stain Fighter® with Baking Soda

Drug Facts

Active ingredient

Sodium Fluoride 0.24% (0.15% w/v fluoride ion)

Purpose

Anticavity

Use

helps protect against cavities

Warnings

Keep out of reach of children under 6 years of age. If more than used for brushing is accidentally swallowed, get medical help or contact a Poison Control Center right away.

Directions

adults and children 2 years of age and older | brush teeth thoroughly, preferably after each meal or at least twice a day, or as directed by a dentist or physician
children 2 to 6 years | use only a pea sized amount and supervise child's brushing and rinsing (to minimize swallowing)
children under 2 years | ask a dentist or physician

Inactive ingredients

Water, Sorbitol, Hydrated Silica, PEG-12, Sodium Lauryl Sulfate, Flavor, Cellulose Gum, Potassium Hydroxide, Tetrasodium Pyrophosphate, Phosphoric Acid, Cocamidopropyl Betaine, Sodium Saccharin, Benzyl Alcohol, Sodium Bicarbonate.

Questions?

1-800-468-6502

Dist. by:
COLGATE-PALMOLIVE CO
New York, NY 10022 U.S.A.

PRINCIPAL DISPLAY PANEL - 85 g Tube Carton

Colgate®

Anticavity Fluoride Toothpaste

Clean Mint Paste

ENAMEL SAFE

Removes 95% of
Daily Surface Stains*
with Micro-Polishing Action

OPTIC
WHITE®

STAIN FIGHTER®
with Baking Soda

NET WT
3.0 OZ (85 g)